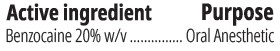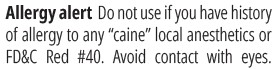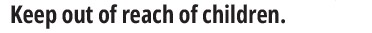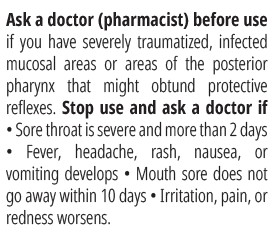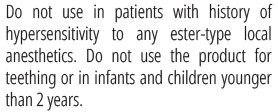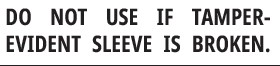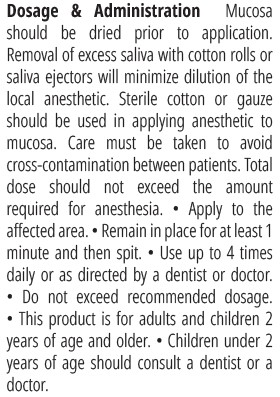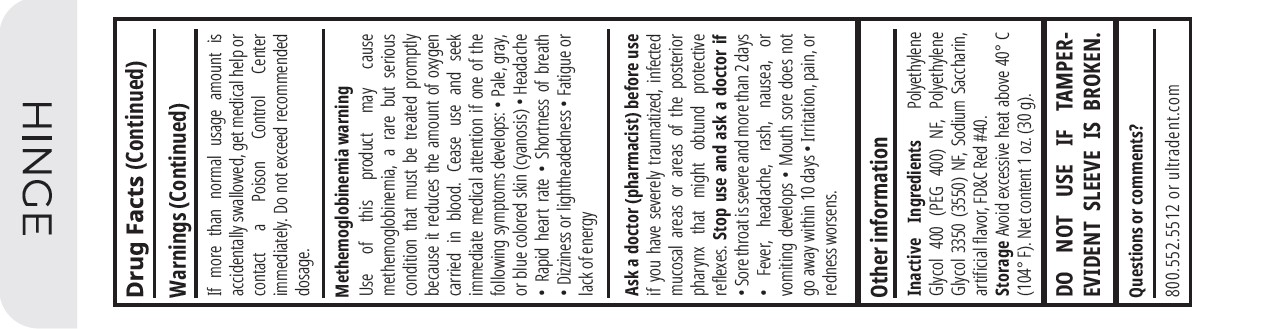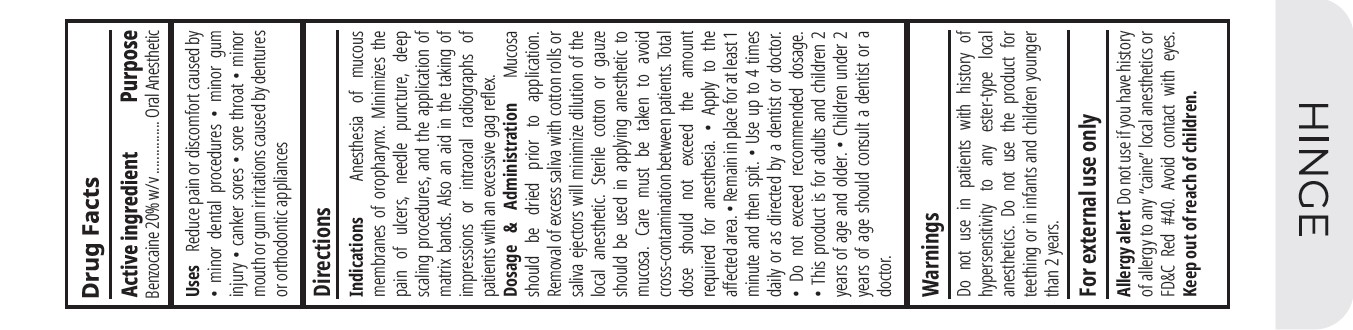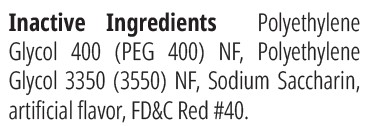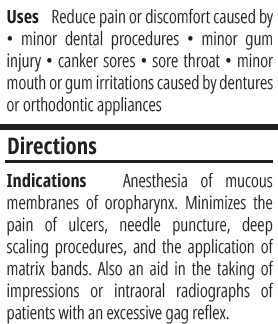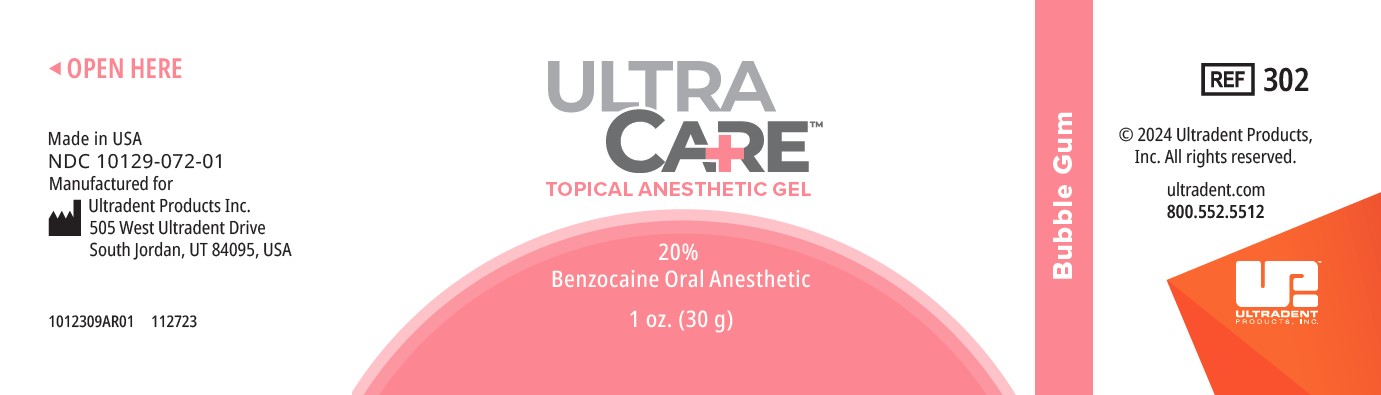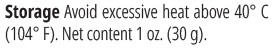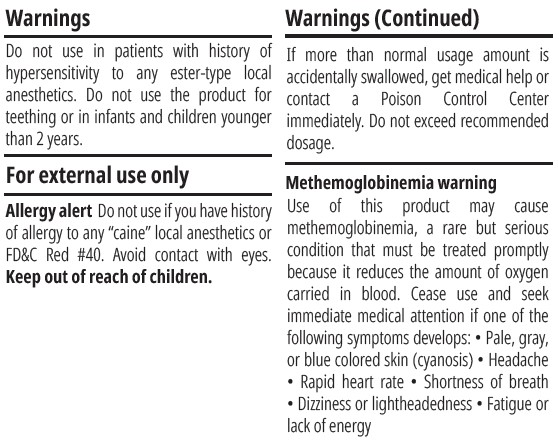 DRUG LABEL: UltraCare Anesthetic Gel
NDC: 10129-072 | Form: GEL
Manufacturer: The Belport Company, Inc. DBA Gingi-Pak
Category: otc | Type: HUMAN OTC DRUG LABEL
Date: 20240320

ACTIVE INGREDIENTS: BENZOCAINE 200 mg/1 g
INACTIVE INGREDIENTS: POLYETHYLENE GLYCOL 3350; POLYETHYLENE GLYCOL 400; POTASSIUM SODIUM SACCHARATE

UltraCare, Bubblegum

Uses

Reduce pain or discomfort caused by minor dental procedures • minor gum injury • canker sores • sore throat • minor mouth or gum irritations caused by dentures or orthodontic appliances.

Keep out of reach of children

DO NOT USE

.

Ask doctor (pharmacist) before use if you have severely traumatized, infected mucosal areas or areas of the posterior pharnx that might obtund protective reflexes. Stop use and ask doctor if sore throat is severe for more than 2 days, fever, headache, rash, nausea, or vomiting develops, mouth sore does not go away within 10 days, irritation, pain or redness worsens.

DOSAGE AND ADMINISTRATION

Mucosa should be dried prior to application. Removal of excess saliva with cotton rolls or saliva ejectors will minimize dilution of the local anethestic. Sterile cotton or gause should be used in applying anesthetic to mucosa. Care must be taken to avoid cross contamination between patients. Total dose should not exceed the amount required for anesthesia. Apply to the affected area. Remain in place for at least 1 minutes and then spit. Use up to 4 times daily or as directed by dentist or doctor. Do not exceed recommended dosage. This product is for adults and children 2 years or age and older. Children under 2 years of age should consult a dentist or a doctor.

INACTIVE INGREDIENT

The inactive ingredients in UltraCare bubblegum are polyethylene glycol 400 (PEG 400) NF, Polyethylene Glycol 3350 (3350) NF, Sodium Saccharin, artificial Flavor, FD$C Red #40.